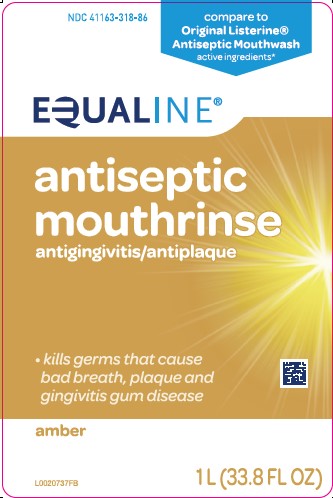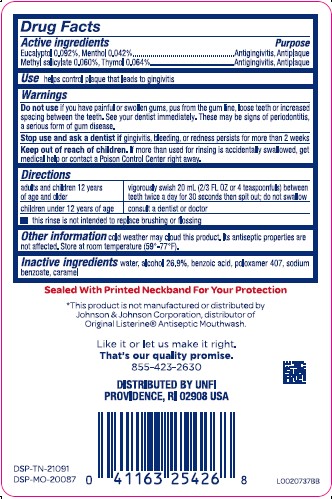 DRUG LABEL: Mouth Rinse
NDC: 41163-318 | Form: MOUTHWASH
Manufacturer: United Natural Foods, Inc. dba UNFI
Category: otc | Type: HUMAN OTC DRUG LABEL
Date: 20260217

ACTIVE INGREDIENTS: EUCALYPTOL 0.92 mg/1 mL; MENTHOL 0.42 mg/1 mL; METHYL SALICYLATE 0.6 mg/1 mL; THYMOL 0.64 mg/1 mL
INACTIVE INGREDIENTS: WATER; ALCOHOL; BENZOIC ACID; POLOXAMER 407; SODIUM BENZOATE; CARAMEL

Equaline 318.003/318AH-AI
Antiseptic Mouthrinse

Active ingredients

Eucalyptol 0.092%

Menthol 0.042%

Methyl salicylate 0.060%

Thymol 0.064%

Purpose

Antigingivitis, Antiplaque

Use

helps control plaque that leads to gingivitis

Warnings

for is product

Do not use

if you have painful or swollen gums, pus from the gum line, loose teeth or increased spacing between the teeth. See your dentist immediately. These may be signs of periodontitis, a serious form of gum disease.

Stop use and ask a dentist if

gingivitis, bleeding, or redness persists for more than 2 weeks

Keep out of reach of children.

If more than used for rinsing is accidentally swallowed, get medical help or contact a Poison Control Center right away.

Directions

adults and children 12 years and older - vigorously swish 20 mL (2/3 FL OZ or 4 teaspoonfuls) between teeth twice a day for 30 seconds then spit out; do not swallow
children under 12 years of age - consult a dentist or doctor

• this rinse is not intended to replace brushing or flossing

Other information

cold weather may cloud this product. Its antiseptic properties are not affected. Store at room temperature (59⁰-77⁰F)

Inactive ingredients

water, alcohol 26.9%, benzoic acid, poloxamer 407, sodium benzoate, caramel

TEP

Sealed With Printed Neckband For Your Protection

Disclaimer

*This product is not manufactured or distributed by Johnson & Johnson Corporation, distributor of Original ListerineAntiseptic Mouthwash.

Adverse reactions

Like it or let us make it right.

That's our quality promise.

855-423-2630

DISTRIBUTED BY UNFI

PROVIDENCE, RI 02908 USA

DSP-TN-21091

DSP-MO-20087

Principal display panel

NDC 41163-318-86

Compare to Oringinal Listerine®Antiseptic Mouthwash active ingredients*

EQUALINE®

antiseptic

mouthrinse

antigingivitis/antiplaque

- kills germs that cause bad breath, plaque and gingivitis gum disease

amber

1 L (33.8 FL OZ)